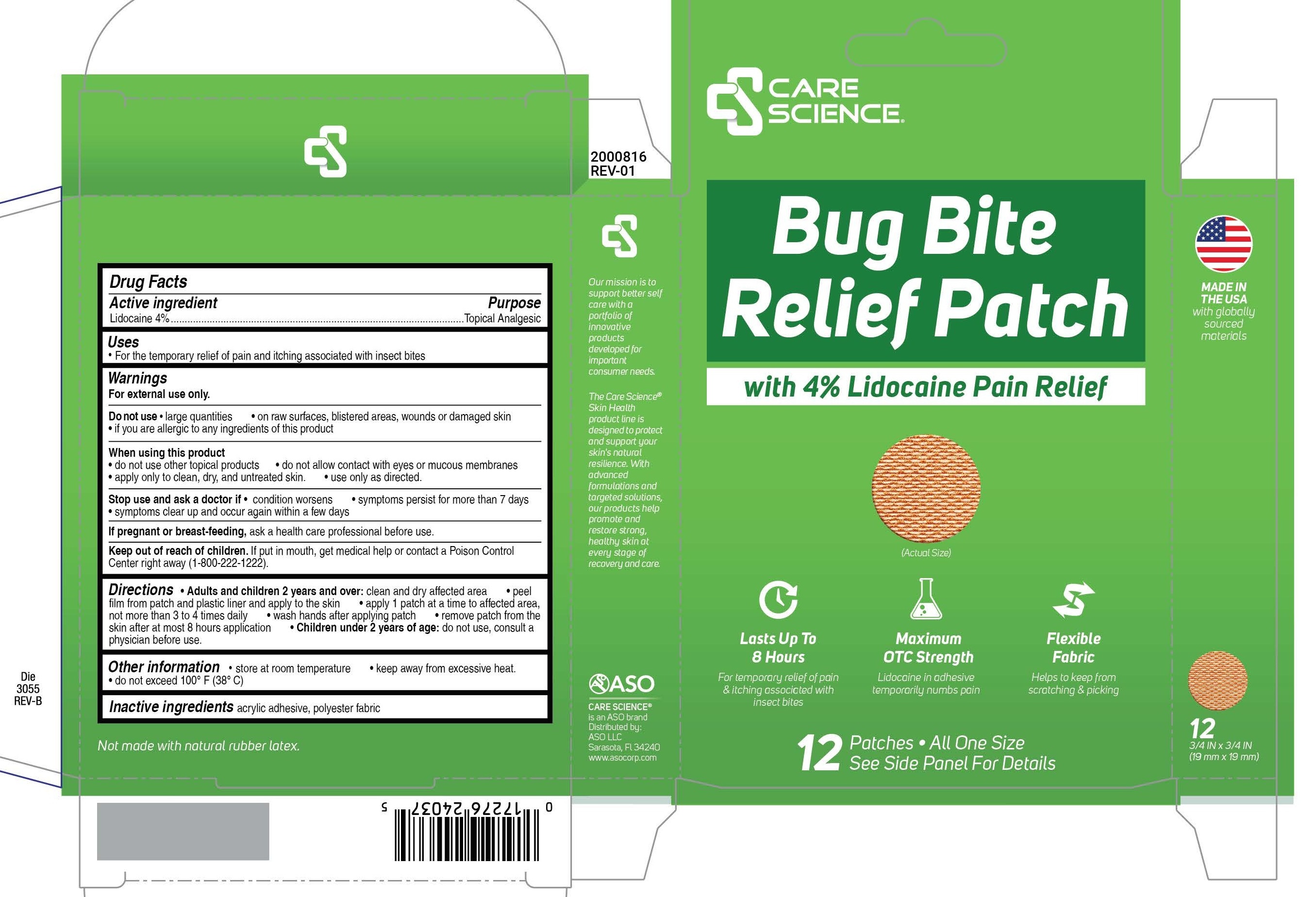 DRUG LABEL: Care Science
NDC: 51142-101 | Form: PATCH
Manufacturer: ASO LLC
Category: otc | Type: HUMAN OTC DRUG LABEL
Date: 20250121

ACTIVE INGREDIENTS: LIDOCAINE 4 mg/100 mg
INACTIVE INGREDIENTS: ETHYLENE-VINYL ACETATE COPOLYMER (15% VINYL ACETATE)

Lidocaine Bug Bite Patch

Active ingredient

Lidocaine 4%

Purpose

Topical Analgesic

Uses

- For the temporary relief of pain and itching associated with insect bites

Warnings

For external use only

Do not use

- large quantities
- on raw surfaces, blistered areas, wounds or damaged skin
- if you are allergic to any ingredients of this product

When using this product

- do not use other topical products
- do not allow contact with eyes or mucous membranes
- apply only to clean, dry, and untreated skin
- use only as directed

Stop use and ask a doctor if

- condition worsens
- symptoms persist for more than 7 days
- symptoms clear up and occur again within a few days

If pregnant or breast-feeding

ask a health care professional before use.

Keep out of reach of children.

If put in mouth, get medical help or contact a Poison Control Center right away (1-800-222-1222).

Directions

- Adults and children 12 years and over: clean and dry affected area
- peel film from patch and plastic liner and apply to the skin
- apply 1 patch at a time to affected area, not more than 3 to 4 times daily
- wash hands after applying patch
- remove patch from the skin after at most 8 hours application
- Children under 12 years of age: do not use, consult a physician before use.

Other information

- Store at room temperature
- keep away from excessive heat
- do not exceed 100oF (38oC)

Inactive ingredients

acrylic adhesive, polyester fabric

Principal Display Panel

CARE SCIENCE

Bug Bite Relief Patch

with 4% Lidocaine Pain Relief

Lats Up to 8 Hours

For temporary relief of pain and itching associated with insects bites

Maximum OTC Strength

Lidocaine in adhesive temporarily numbs pain

Flexible Fabric

Helps to keep from scratching and picking

12 Patches All one Size

See side Panel for Details